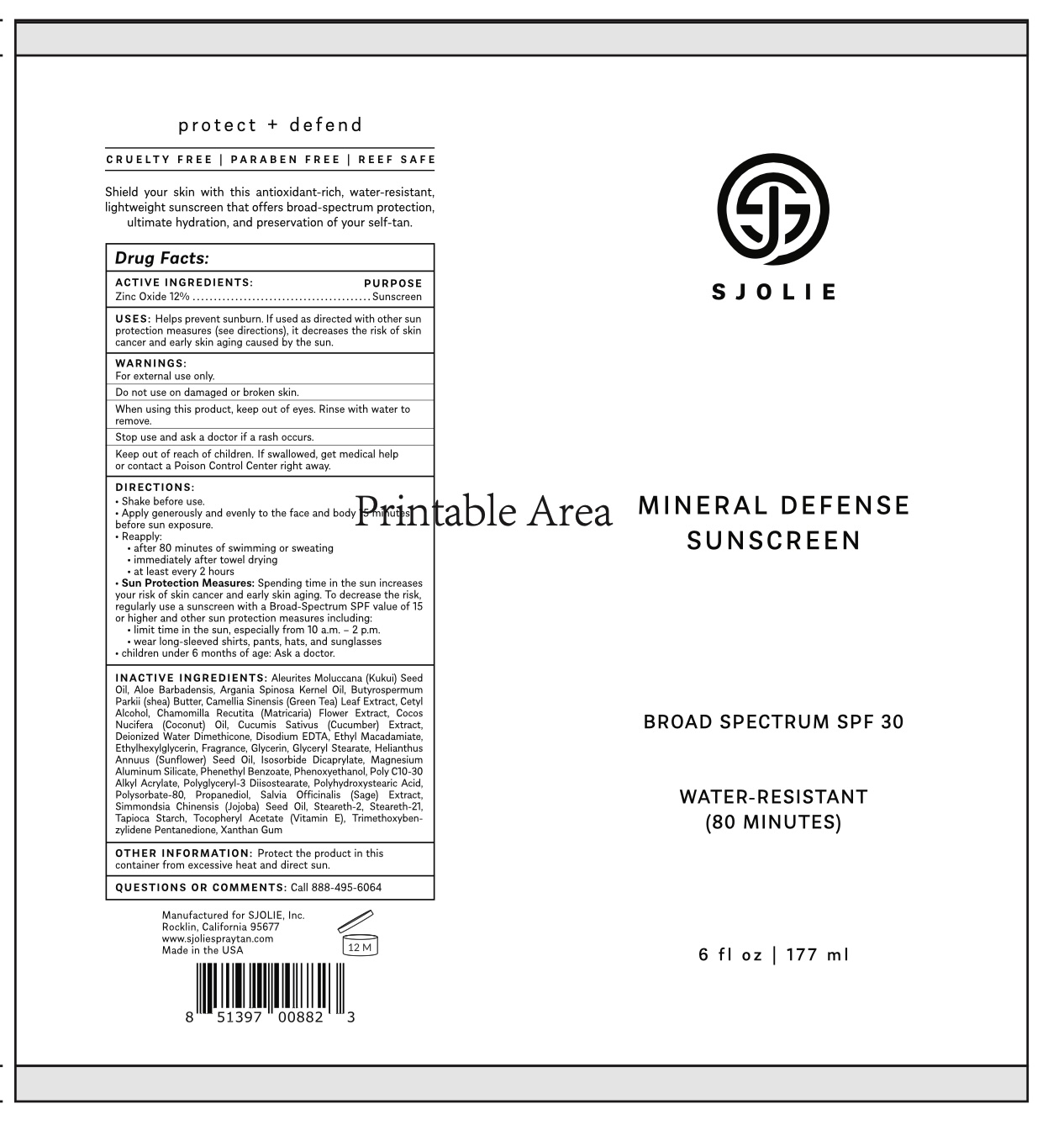 DRUG LABEL: Sjolie Tanning SPF 30 Sunscreen
NDC: 85947-001 | Form: CREAM
Manufacturer: SJOLIE, INC.
Category: otc | Type: HUMAN OTC DRUG LABEL
Date: 20250717

ACTIVE INGREDIENTS: ZINC OXIDE 11 g/100 g
INACTIVE INGREDIENTS: ALOE BARBADENSIS LEAF JUICE; BUTYROSPERMUM PARKII (SHEA) BUTTER; CETYL ALCOHOL; COCOS NUCIFERA (COCONUT) OIL; CUCUMIS SATIVUS (CUCUMBER) JUICE; TROMETHAMINE MAGNESIUM ALUMINUM SILICATE; PHENETHYL BENZOATE; POLYHYDROXYSTEARIC ACID (2300 MW); PHENOXYETHANOL; ACRYLATES/C10-30 ALKYL ACRYLATE CROSSPOLYMER (60000 MPA.S); POLYGLYCERYL-3 DIISOSTEARATE; POLYSORBATE 80; STEARETH-21; CAMELLIA SINENSIS LEAF; ETHYL MACADAMIATE; ISOSORBIDE DICAPRYLATE; SALVIA OFFICINALIS (SAGE) OIL; TAPIOCA STARCH; TRIMETHOXYBENZYLIDENE PENTANEDIONE; EDETATE DISODIUM; ETHYLHEXYLGLYCERIN; ALPHA-TOCOPHEROL; XANTHAN GUM; ALEURITES MOLUCCANA SEED; MATRICARIA CHAMOMILLA FLOWERING TOP OIL; GLYCERIN; GLYCERYL STEARATE; HELIANTHUS ANNUUS (SUNFLOWER) SEED OIL; STEARETH-2; WATER; DIMETHICONE 350; SIMMONDSIA CHINENSIS (JOJOBA) SEED OIL; ARGANIA SPINOSA KERNEL OIL; PROPANEDIOL

Sjolie Tanning SPF 30 Lotion

ACTIVE INGREDIENT

Zinc Oxide 12%

PURPOSE

Sunscreen

USES

Helps prevent sunburn. If used as directed with other sun protection measures (see directions), it decreases the risk of skin cancer and early skin aging caused by the sun.

WARNINGS

For external use only.

Do not use on damaged or broken skin.

When using this product, keep out of eyes. Rinse with water to remove.

Stop use and ask a doctor if a rash occurs.

Keep out of reach of children

If swallowed, get medical help or contact a Poison Control Center right away.

DIRECTIONS

Shake before use.
Apply generously and evenly to the face and body before sun exposure.
Reapply:
after 80 minutes of swimming or sweating
immediately after towel drying
at least every 2 hours
Sun Protection Measures: Spending time in the sun increases your risk of skin cancer and early skin aging. To decrease the risk, regularly use a sunscreen with a Broad-Spectrum SPF value of 15 or higher and other sun protection measures including:
limit time in the sun, especially from 10 a.m. - 2 p.m.
wear long-sleeved shirts, pants, hats, and sunglasses
children under 6 months of age: Ask a doctor.

INACTIVE INGREDIENTS

Aleurites Moluccana (Kukui) Seed Oil, Aloe Barbadensis, Argania Spinosa Kernel Oil, Butyrospermum Parkii (shea) Butter, Camellia Sinensis (Green Tea) Leaf Extract, Cetyl Alcohol, Chamomilla Recutita (Matricaria) Flower Extract, Cocos Nucifera (Coconut) Oil, Cucumis Sativus (Cucumber) Extract, Deionized Water Dimethicone, Disodium EDTA, Ethyl Macadamiate, Ethylhexylglycerin, Fragrance, Glycerin, Glyceryl Stearate, Helianthus Annuus (Sunflower) Seed Oil, Isosorbide Dicaprylate, Magnesium Aluminum Silicate, Phenethyl Benzoate, Phenoxyethanol, Poly C10-30 Alkyl Acrylate, Polyglyceryl-3 Diisostearate, Polyhydroxystearic Acid, Polysorbate-80, Propanediol, Salvia Officinalis (Sage) Extract, Simmondsia Chinensis (Jojoba) Seed Oil, Steareth-2, Steareth-21, Tapioca Starch, Tocopheryl Acetate (Vitamin E), Trimethoxyben-zylidene Pentanedione, Xanthan Gum

OTHER INFORMATION

Protect the product in this container from excessive heat and direct sun.

QUESTIONS OR COMMENTS

Call 888-495-6064